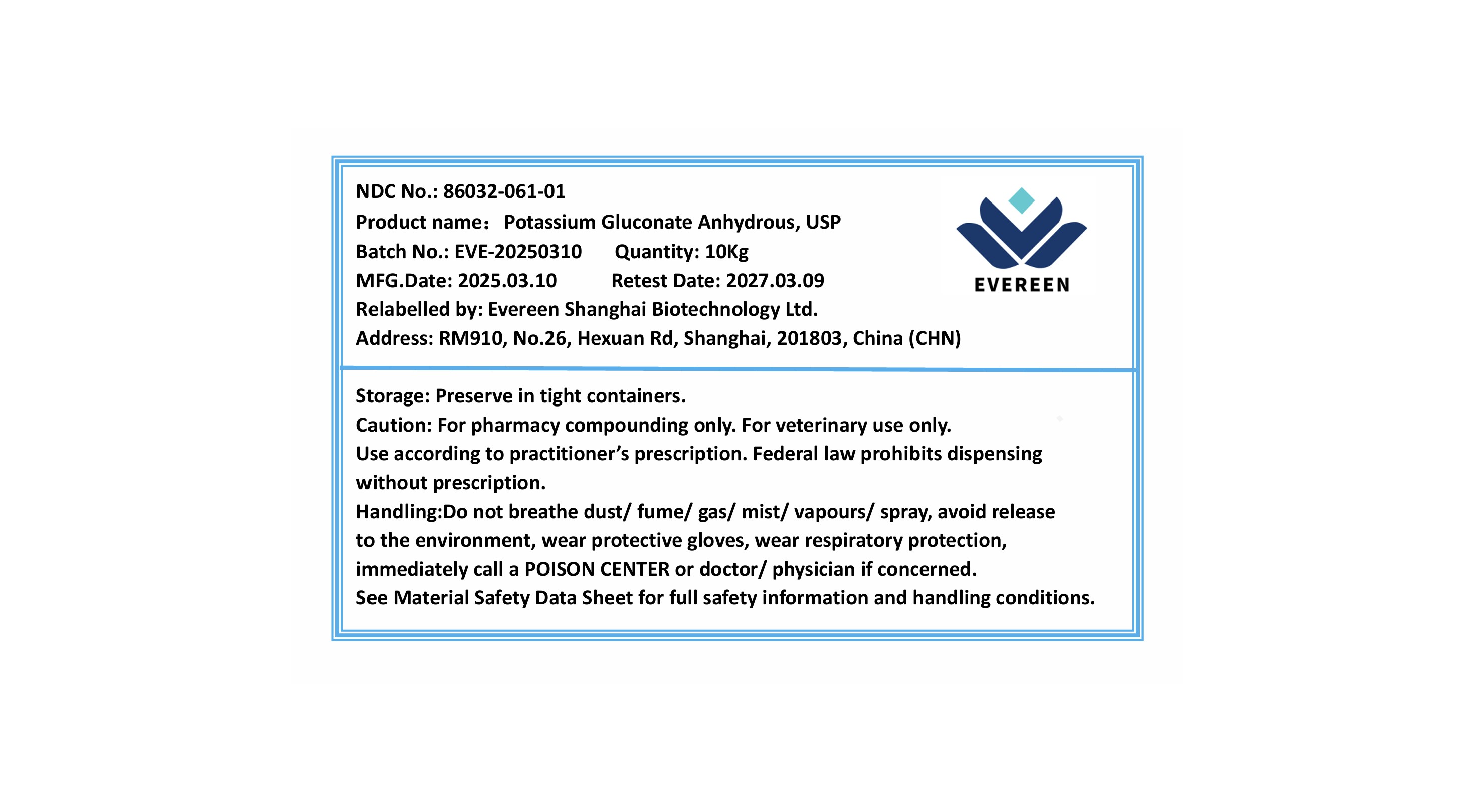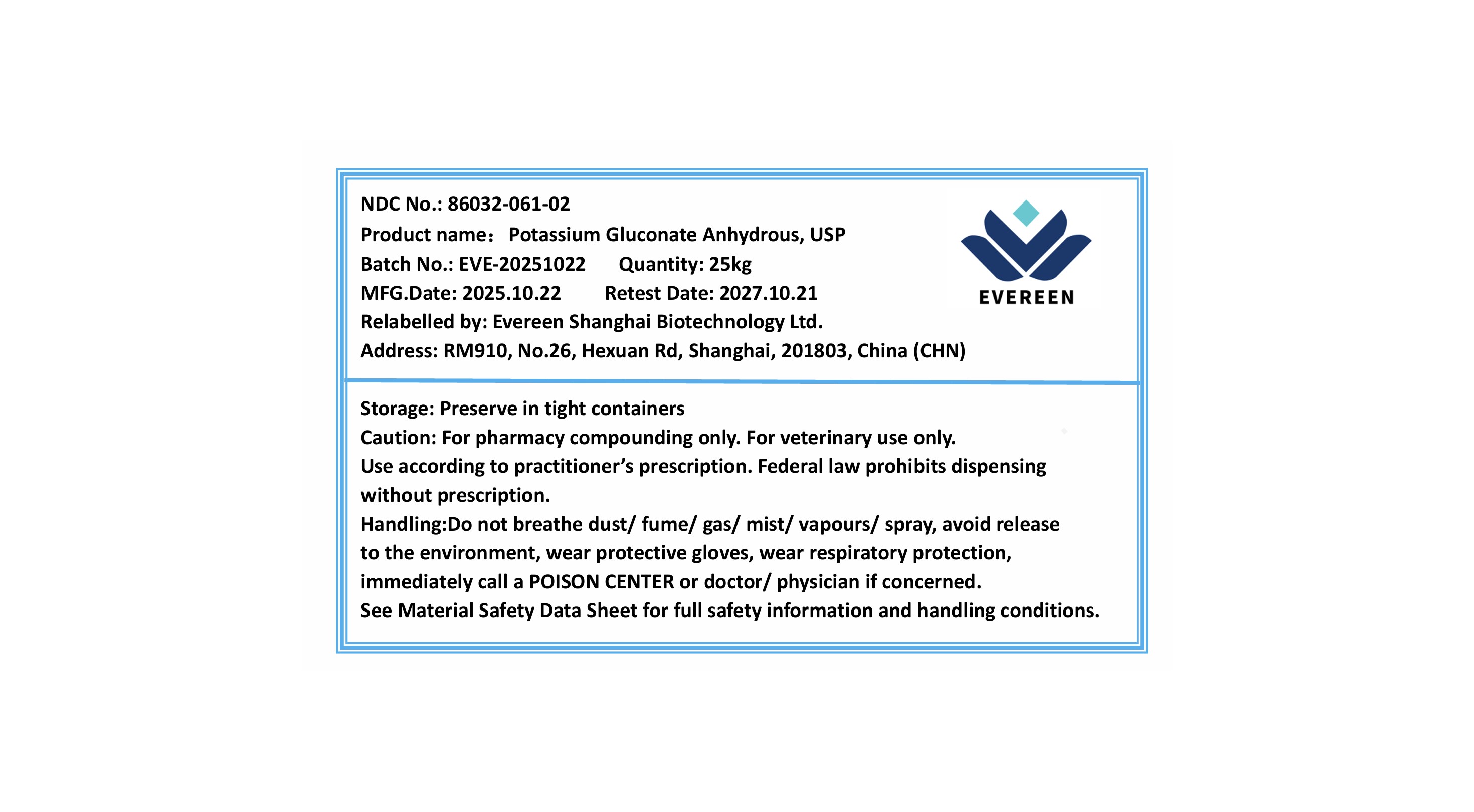 DRUG LABEL: Potassium Gluconate Anhydrous
NDC: 86032-061 | Form: POWDER
Manufacturer: Evereen Shanghai Biotechnology Ltd.
Category: other | Type: BULK INGREDIENT - ANIMAL DRUG
Date: 20251106

ACTIVE INGREDIENTS: POTASSIUM GLUCONATE 1 kg/1 kg

Potassium Gluconate Anhydrous